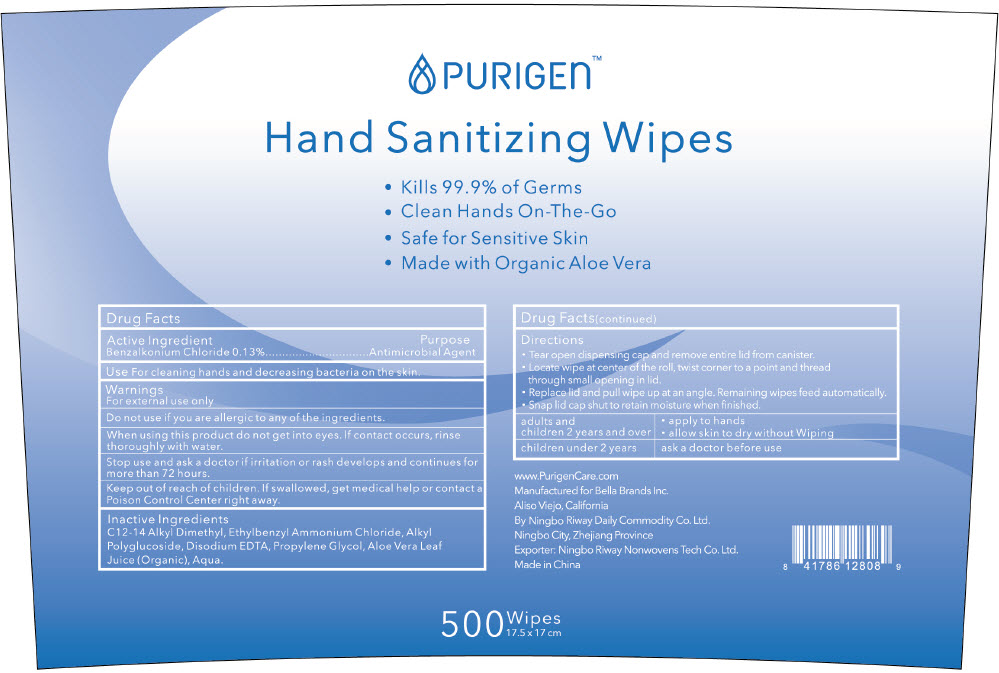 DRUG LABEL: Hand Sanitizing Wipes
NDC: 80994-005 | Form: CLOTH
Manufacturer: BELLA BRANDS INC
Category: otc | Type: HUMAN OTC DRUG LABEL
Date: 20201119

ACTIVE INGREDIENTS: BENZALKONIUM CHLORIDE 1.3 mg/1 mL
INACTIVE INGREDIENTS: Edetate Disodium Anhydrous; Propylene Glycol; Aloe Vera Leaf; Water

Hand Sanitizing Wipes

Drug Facts:

Active Ingredient

Benzalkonium Chloride, 0.13%

Purpose

Antimicrobial Agent

Use

for cleaning hands and decreasing bacteria on the skin.

Warnings

- For external use only.

- Do not use if you are allergic to any of the ingredients.

- When using this product, do not get into eyes. If contact occurs, rinse thoroughly with water.

- Stop use and consult a doctor if irritation or rash develops and continues for more than 72 hours.

- Keep out of reach of children. If swallowed, get medical help or visit a Poison Control Center right away.

Inactive Ingredients

C12-14 Alkyl Dimethyl, Ethylbenzyl Ammonium Chloride, Alkyl Polyglucoside, Disodium EDTA, Propylene Glycol, Aloe Vera Leaf Juice (Organic), Aqua.

Directions For Use

- Press dispensing pump to release product into hands, add water and rub thoroughly around both sides of hands and between fingers. Rinse off and towel dry.

- For adults and children 2 years and over.

- For children under 2 years of age, consult a doctor before use.

Directions

- Tear open dispensing cap and remove entire lid from canister.
- Locate wipe at center of the roll, twist corner to a point and thread through small opening in lid.
- Replace lid and pull wipe up at an angle. Remaining wipes feed automatically.
- Snap lid cap shut to retail moisture when finished.
  Adults and children 2 years and over
  Apply to hands, Allow skin to dry without wiping
  Children under 2 years, ask a doctor before use

Manufactured for Bella Brands Inc.
Aliso Viejo, California
By Ningbo Riway Daily Commodity Co Ltd.
Ningbo City, Zhejiang Province

PRINCIPAL DISPLAY PANEL - 500 Wipe Canister Label

PURIGEN™
Hand Sanitizing Wipes

- Kills 99.9% of Germs
- Clean Hands On-The-Go
- Safe for Sensitive Skin
- Made with Organic Aloe Vera

500
Wipes
17.5 x 17 cm